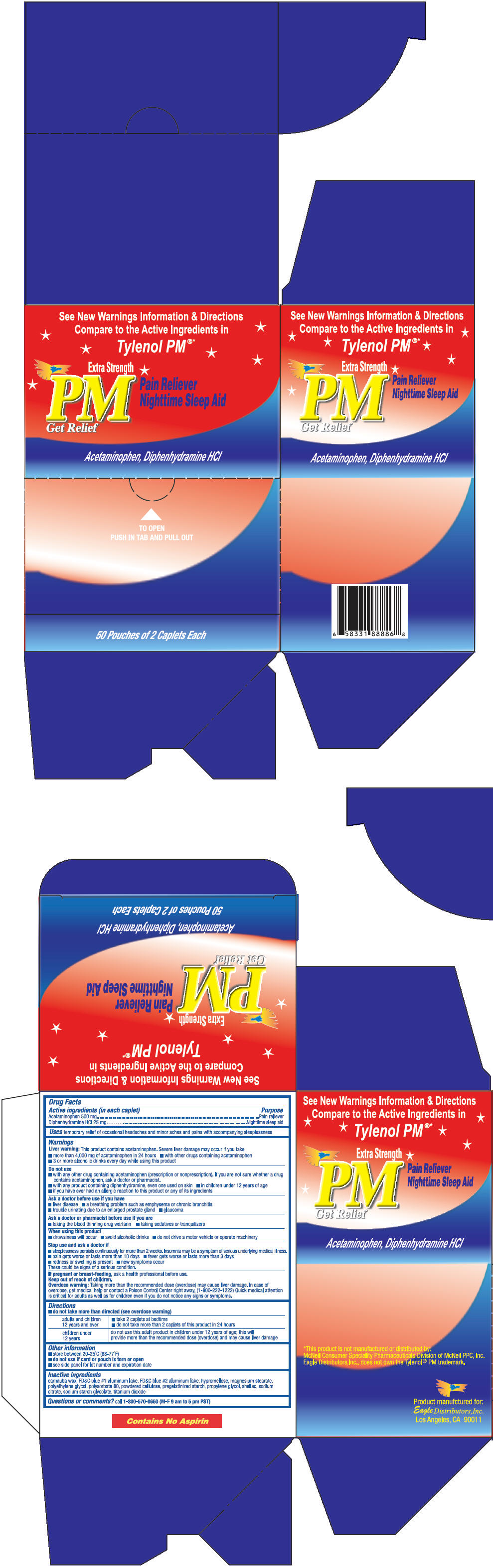 DRUG LABEL: PM Get Relief
NDC: 68737-224 | Form: TABLET
Manufacturer: Eagle Distributors,Inc.
Category: otc | Type: HUMAN OTC DRUG LABEL
Date: 20120611

ACTIVE INGREDIENTS: Acetaminophen 500 mg/1 1; Diphenhydramine Hydrochloride 25 mg/1 1
INACTIVE INGREDIENTS: croscarmellose sodium; FD&C blue no. 1; hypromelloses; cellulose, microcrystalline; polyethylene glycols; povidone; stearic acid; titanium dioxide; polyvinyl alcohol; silicon dioxide; talc

PM Get Relief

Drug Facts

ACTIVE INGREDIENT

PURPOSE

Active ingredients (in each caplet) | Purposes
Acetaminophen 500 mg | Pain reliever
Diphenhydramine HCl 25 mg | Nighttime sleep aid

Uses

temporarily relieves occasional headaches and minor aches and pains with accompanying sleeplessness

Warnings

Liver warning

This product contains acetaminophen. Severe liver damage may occur if you take

- more than 4,000 mg of acetaminophen in 24 hours
- with other drugs containing acetaminophen
- 3 or more alcoholic drinks every day while using this product

Do not use

- with any other drug containing acetaminophen (prescription or nonprescription). If you are not sure whether a drug contains acetaminophen, ask a doctor or pharmacist.
- with any product containing diphenhydramine, even one used on skin
- in children under 12 years of age
- if you have ever had an allergic reaction to this product or any of its ingredients

Ask a doctor before use if you have

- liver disease
- a breathing problem such as emphysema or chronic bronchitis
- trouble urinating due to an enlarged prostate gland
- glaucoma

Ask a doctor or pharmacist before use if you are

- taking the blood thinning drug warfarin
- taking sedatives or tranquilizers

When using this product

- drowsiness will occur
- avoid alcoholic drinks
- do not drive a motor vehicle or operate machinery

Stop use and ask a doctor if

- sleeplessness persists continuously for more than 2 weeks. Insomnia may be a symptom of serious underlying medical illness.
- pain gets worse or lasts more than 10 days
- fever gets worse or lasts more than 3 days
- redness or swelling is present
- new symptoms occur

These could be signs of a serious condition.

PREGNANCY OR BREAST FEEDING

If pregnant or breast-feeding, ask a health professional before use.

Keep out of reach of children.

Overdose warning

Taking more than the recommended dose (overdose) may cause liver damage. In case of overdose, get medical help or contact a Poison Control Center right away. (1-800-222-1222) Quick medical attention is critical for adults as well as for children even if you do not notice any signs or symptoms.

Directions

Adults and children 12 years of age and over | Take 2 caplets at bedtime. Do not take more than 2 caplets of this product in 24 hours.
Children under 12 years of age | Do not use this adult strength product. This will provide more than the recommended dose (overdose) and could cause serious health problems

Other information

- store between20-25 C (68-77 F)
- do not use if pouch is torn or open

Inactive ingredients

croscarmellose sodium, FD&C blue #1, hypromellose, microcrystalline cellulose, polyethylene glycol, povidone, starch, stearic acid, titanium dioxide. May contain polyvinyl alcohol, silicon dioxide, sodium starch glycolate, talc.

Questions or comments?

Call 1-800-570-8650 (M-F 9am to 5pm PST)

Product manufactured for:
Eagle Distributors,Inc.
Los Angeles, CA 90011

PRINCIPAL DISPLAY PANEL - 50 Pouch Carton

See New Warnings Information & Directions
Compare to the Active Ingredients in
Tylenol PM®*

Extra Strength
PM
Get Relief
Pain Reliever
Nighttime Sleep Air

Acetaminophen, Diphenhydramine HCI